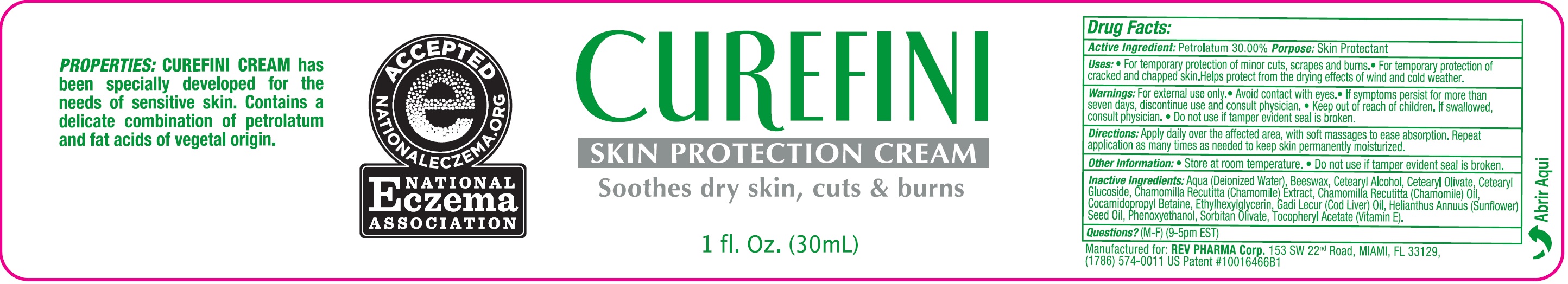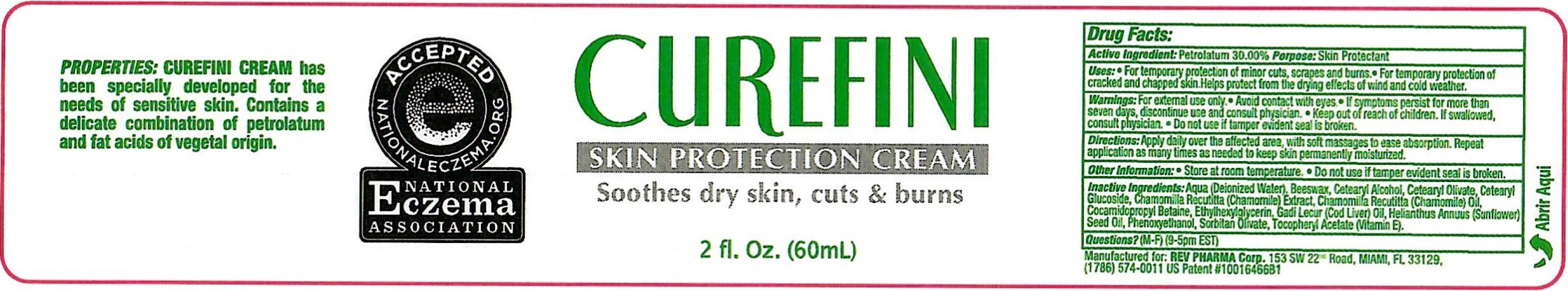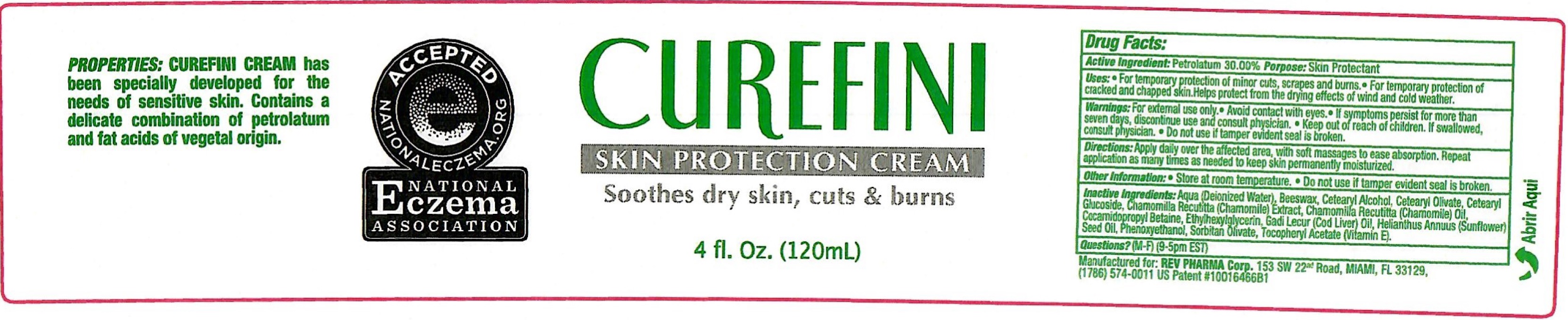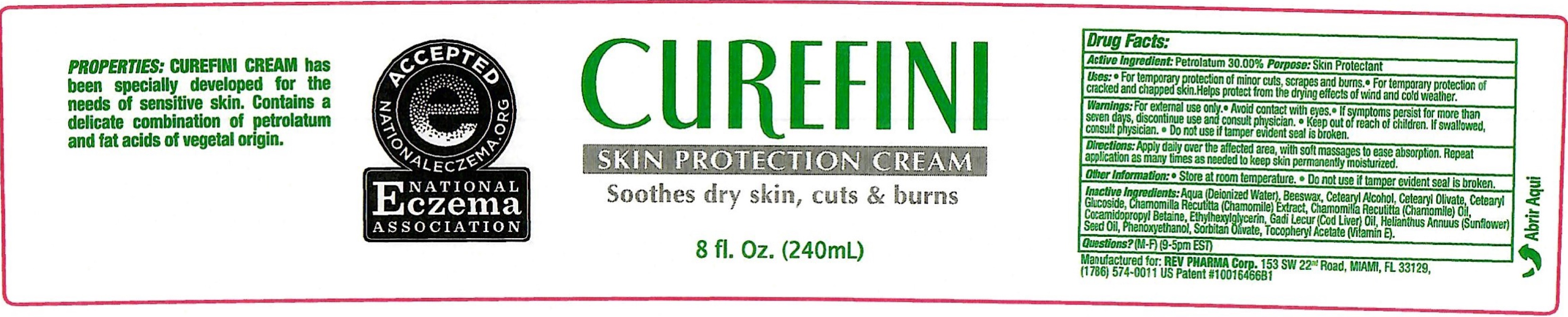 DRUG LABEL: CUREFINI Skin Protection Cream
NDC: 69981-194 | Form: CREAM
Manufacturer: Rev Pharma Corp
Category: otc | Type: HUMAN OTC DRUG LABEL
Date: 20260119

ACTIVE INGREDIENTS: PETROLATUM 300 mg/1 mL
INACTIVE INGREDIENTS: WATER; YELLOW WAX; CETOSTEARYL ALCOHOL; CETEARYL OLIVATE; CETEARYL GLUCOSIDE; CHAMOMILE; COCAMIDOPROPYL BETAINE; ETHYLHEXYLGLYCERIN; COD LIVER OIL; SUNFLOWER OIL; PHENOXYETHANOL; SORBITAN OLIVATE; .ALPHA.-TOCOPHEROL ACETATE

CUREFINI Skin Protection Cream

Active Ingredient:

Petrolatum 30.00%

Porpose:

Skin Protectant

Uses:

- For the temporary protection of minor cuts, scrapes and burns.
- For temporary protection of cracked and chapped skin.Helps protect from the drying effects of wind and cold weather.

Warnings:

For external use only. •Avoid contact with eyes. • If symptoms persist for more than seven days, discontinue use and consult a physician.

Keep out of reach of children.

- If swallowed, consult physician.

Do not use

- if tamper evident seal is broken.

Directions:

Apply daily over the affected area, with soft massages to ease absorption. Repeat application as many times as needed to keep skin permanently moisturized.

Other Information:

- Store at room temperature.
- Do not use if tamper evident seal is broken.

Inactive Ingredients:

Aqua (Deionized Water), Beeswax, Cetearyl Alcohol, Cetearyl Olivate, Cetearyl Glucoside, Chamomilla Recutitta (Chamomile) Extract, Chamomilla Recutitta (Chamomile) Oil, Cocamidopropyl Betaine, Ethylhexylglycerin, Gadi Lecur (Cod Liver) Oil, Helianthus Annuus (Sunflower) Seed Oil, Phenoxyethanol, Sorbitan Olivate, Tocopheryl Acetate (Vitamin E).

Questions?

(M-F) (9-5pm EST)